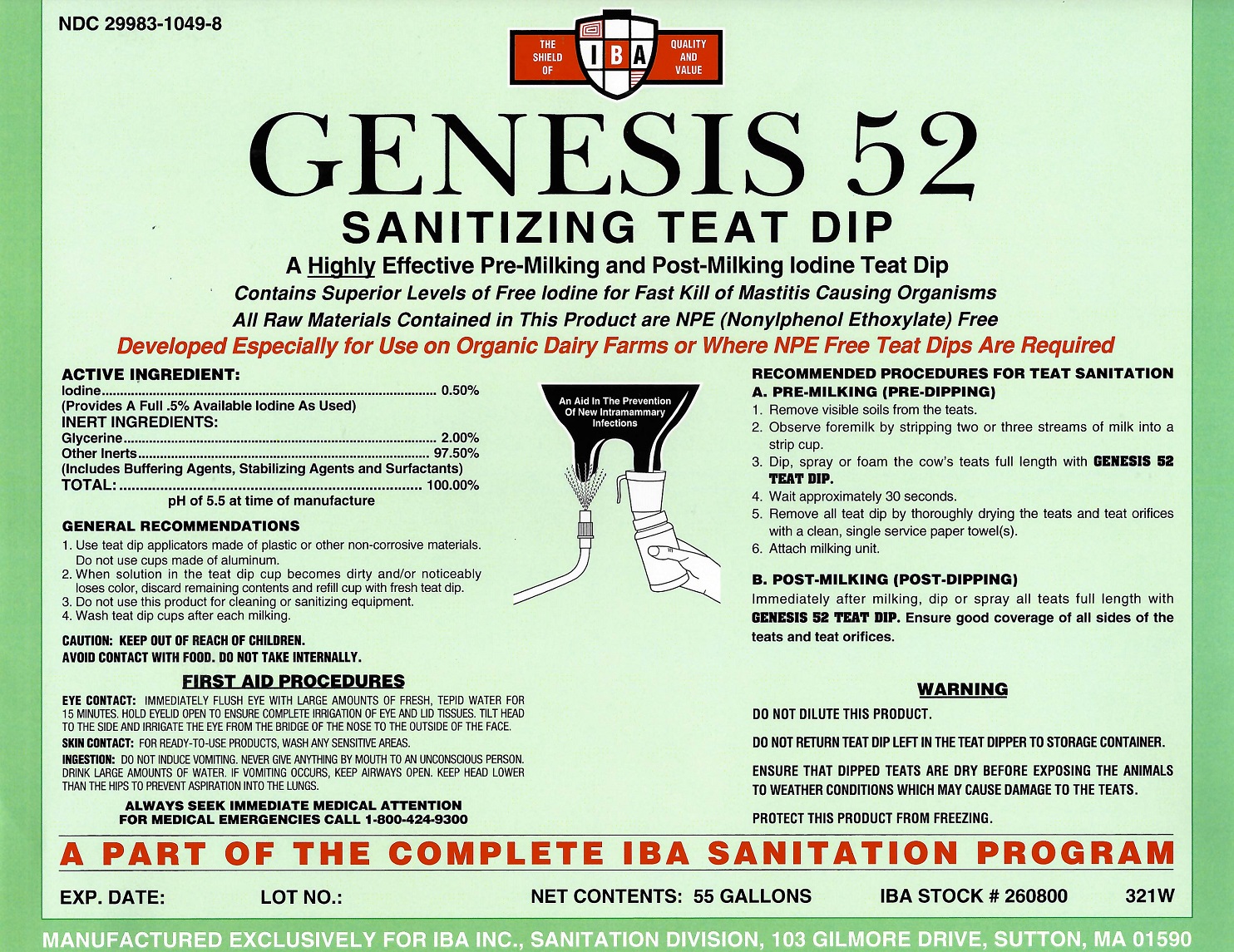 DRUG LABEL: Genesis 52
NDC: 29983-1049 | Form: LIQUID
Manufacturer: IBA
Category: animal | Type: OTC ANIMAL DRUG LABEL
Date: 20251126

ACTIVE INGREDIENTS: IODINE 0.50 kg/100 kg

Genesis 52

ACTIVE INGREDIENT

Iodine..............................................................0.50%

INERT INGREDIENTS

Glycerine.........................................................2.00%

Other Inerts.....................................................97.50%

(Incudes Buffering Agents, Stabilizing Agents and Surfactants)

TOTAL..............................................................100%

pH of 5.5 at time of manufacture

GENERAL RECOMMENDATIONS

1. Use teat dip applicators made of plastic or other non-corrosive materials. Do not use cups made of aluminum.

2. When solution in the teat dip cup becomes dirty and/or noticeably loses color, discard remaining contents and refill cup with fresh teat dip.

3. Do not use this product for cleaning or sanitizing equipment.

4. Wash teat dip cups after each milking

CAUTION: KEEP OUT OF REACH OF CHILDREN.

AVOID CONTACT WITH FOOD. DO NOT TAKE INTERNALLY.

FIRST AID PROCEDURES

EYE CONTACT: IMMEDIATELY FLUSH EYE WITH LARGE AMOUNTS OF FRESH, TEPID WATER FOR 15 MINUTES. HOLD EYELID OPEN TO ENSURE COMPLETE IRRIGATION OF EYE AND LID TISSUES. TILT HEAD TO THE SIDE AND IRRIGATE THE EYE FROM THE BRIDGE OF THE NOSE TO THE OUTSIDE OF THE FACE.

SKIN CONTACT: FOR READY-TO-USE PRODUCTS, WASH ANY SENSITIVE AREAS.

INGESTION: DO NOT INDUCE VOMITING. NEVER GIVE ANYTHING BY MOUTH TO AN UNCONSCIOUS PERSON. DRINK LARGE AMOUNTS OF WATER. IF VOMITING OCCURS, KEEP AIRWAYS OPEN. KEEP HEAD LOWER THAN THE HIPS TO PREVENT ASPIRATION INTO THE LUNGS.

ALWAYS SEEK IMMEDIATE MEDICAL ATTENTION

FOR MEDICAL EMERGENCIES CALL 1-800-424-9300

RECOMMENDED PROCEDURES FOR TEAT SANITATION

A. PRE-MILKING (PRE-DIPPING)

1. Remove visible soils from the teats.

2. Observe foremilk by stripping two or three streams of milk into a strip cup.

3. Dip or spray the cow's teats full length with GENESIS 52 TEAT DIP.

4. Wait approximately 30 seconds

5. Remove all teat dip by thoroughly drying the teats and teat orifices with a clean, single service paper towels(s)

6. Attach milking kit

B. POST-MILKING (POST-DIPPING)

Immediately after milking, dip or spray all teats full length with GENESIS 52 TEAT DIP. Ensure good coverage of all sides of the teats and teat orifices.

WARNING

DO NOT DILUTE THIS PRODUCT.

DO NOT RETURN TEAT DIP LEFT IN THE TEAT DIPPER TO STORAGE CONTAINER.

ENSURE THAT DIPPED TEATS ARE DRY BEFORE EXPOSING THE ANIMALS TO WEATHER CONDITIONS WHICH MAY CAUSE DAMAGE TO THE TEATS. PROTECT THIS PRODUCT FROM FREEZING.

*SPECIAL NOTE TO PROCEDURES

AS WITH ANY PRODUCT, CHECK WITH

YOUR USDA APPROVED ORGANIC

CERTIFICATION AGENCY BEFORE USE.